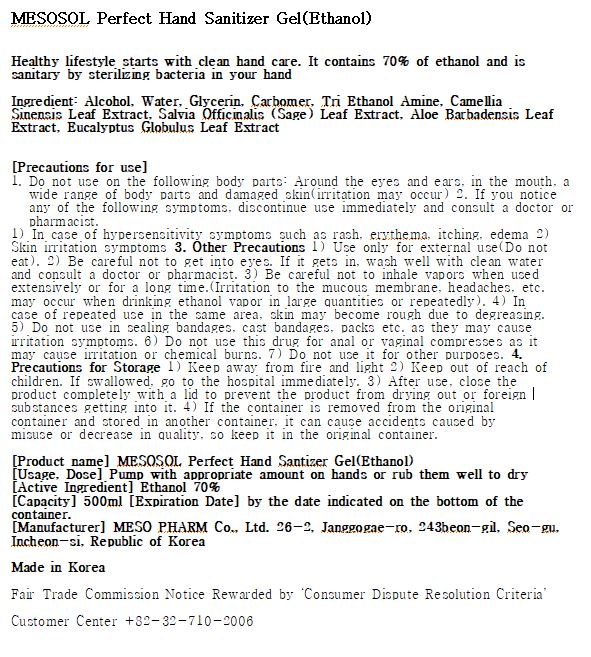 DRUG LABEL: MESOSOL Perfect Hand Sanitizer gel
NDC: 77098-0001 | Form: GEL
Manufacturer: MESO PHARM CO LTD
Category: otc | Type: HUMAN OTC DRUG LABEL
Date: 20200430

ACTIVE INGREDIENTS: ALCOHOL 70 mL/100 mL
INACTIVE INGREDIENTS: TROLAMINE; GLYCERIN; CARBOMER 940; ALOE VERA LEAF; WATER

Drug Facts

ACTIVE INGREDIENT

alcohol

INACTIVE INGREDIENT

Water, Glycerin, Carbomer, Tri Ethanol Amine, Camellia Sinensis Leaf Extract, Salvia Officinalis (Sage) Leaf Extract, Aloe Barbadensis Leaf Extract, Eucalyptus Globulus Leaf Extract

PURPOSE

Sterilization of hands and skin

KEEP OUT OF REACH OF THE CHILDREN

INDICATIONS AND USAGE

Apply to clean, dry hands. Apply sufficient amount to thoroughly wet all surfaces of hands and fingers. Rub onto hands until dry.

Supervise children in the use of this product.

WARNINGS

■ Flammable. Keep away from fire or flame.

■ For external use only.

■ Do not use in eyes.

■ lf swallowed, get medical help promptly.

■ Stop use, ask doctor lf irritation occurs.

■ Keep out of reach of children.

DOSAGE AND ADMINISTRATION

for external use only